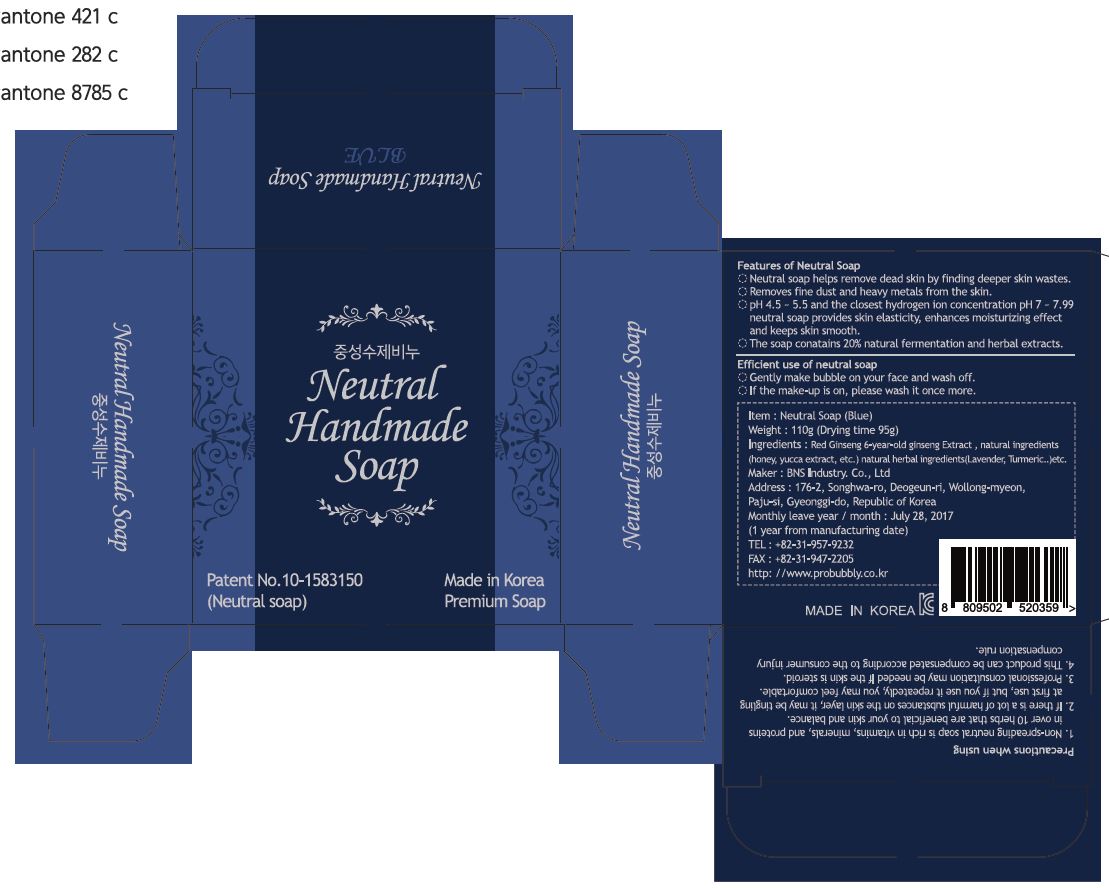 DRUG LABEL: Neutral handmade Blue
NDC: 71657-0001 | Form: SOAP
Manufacturer: BNS Industry Co., Ltd.
Category: otc | Type: HUMAN OTC DRUG LABEL
Date: 20170817

ACTIVE INGREDIENTS: HONEY 8 g/110 g
INACTIVE INGREDIENTS: ORANGE OIL; LAVENDER OIL; LEMON OIL

Drug Facts

ACTIVE INGREDIENT

honey

INACTIVE INGREDIENT

soap base, red ginseng, lemon oil, orange oil, lavender oil, etc

PURPOSE

Neutral soap helps remove dead skin by finding deeper skin wastes.

Removes fine dust and heavy metals from the skin.

PH 4.5 ~ 5.5 and the closest hydrogen ion concentration pH 7 ~ 7.99 neutral soap provides skin elasticity, enhances moisturizing effect and keeps skin smooth.

The soap conatains 20% natural fermentation and herbal extracts.

keep out of reach of the children

INDICATIONS AND USAGE

Efficient use of neutral soap

Gently make bubble on your face and wash off

If the make-up is on, please wash it once more.

WARNINGS

Precautions when using

1. Non-spreading neutral soap is rich in vitamins, minerals, and proteins in over 10 herbs that are beneficial to your skin and balance.

2. If there is a lot of harmful substances on the skin layer, it may be tingling at first use, but if you use it repeatedly, you may feel comfortable.

3. Professional consultation may be needed If the skin is steroid.

4. This product can be compensated according to the consumer injury compensation rule.

DOSAGE AND ADMINISTRATION

for external use only